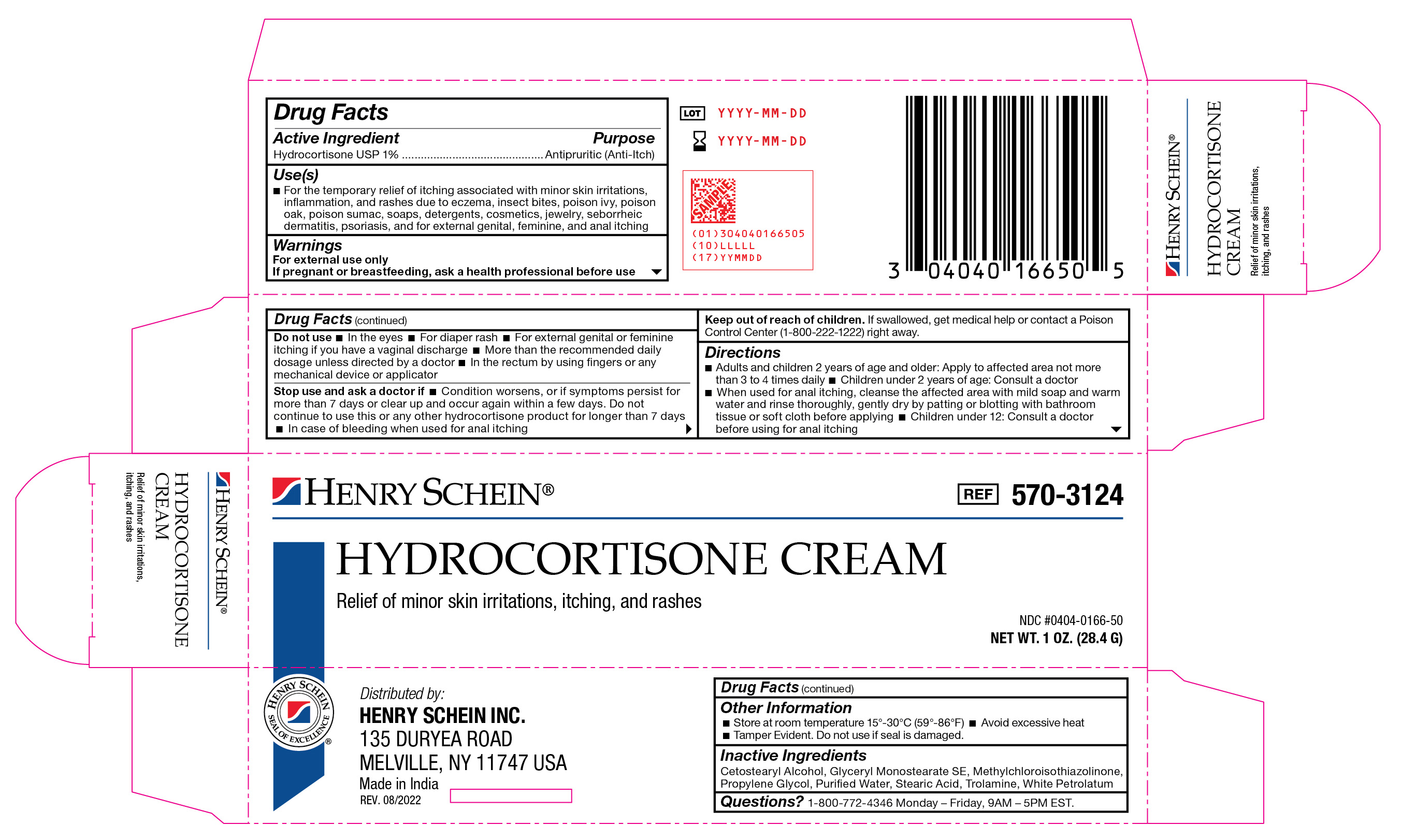 DRUG LABEL: Hydrocortisone
NDC: 0404-0166 | Form: CREAM
Manufacturer: Henry Schein
Category: otc | Type: HUMAN OTC DRUG LABEL
Date: 20251125

ACTIVE INGREDIENTS: HYDROCORTISONE 1 g/100 g
INACTIVE INGREDIENTS: GLYCERYL MONOSTEARATE; METHYLCHLOROISOTHIAZOLINONE; WATER; TROLAMINE; CETOSTEARYL ALCOHOL; PROPYLENE GLYCOL; WHITE PETROLATUM; STEARIC ACID

570-3124 Hydrocortisone Cream 1% NDC 0404-0166-50

Active Ingredient

Hydrocortisone USP 1%

Purpose

Antipruritic (Anti-Itch)

Use(s)

For the temporary relief of itching associated with minor skin irritations, inflammation, and rashes due to eczema, insect bites, poison ivy, poison oak, poison sumac, soaps, detergents, cosmetics, jewelry, seborrheic dermatitis, psoriasis, and for external genital, feminine, and anal itching.

Warnings

For External Use Only

If pregnant or breastfeeding, ask a health professional before use

Do not use

• In the eyes

• For diaper rash

• For external genital or feminine itching if you have a vaginal discharge

• More than the recommended daily dosage unless directed by a doctor

• In the rectum by using fingers or any mechanical device or applicator

Stop use and ask a doctor if

• Condition worsens or if symptoms persist for more than 7 days or clear up and occur again within a few days. Do not continue to use this or any other hydrocortisone product for longer that 7 days

• In case of bleeding when used for anal itching

Keep out of reach of children

If swallowed, get medical help or contact a Poison Control Center (1-800-222-1222) right away.

Directions

• Adults and children 2 years of age and older: Apply to affected area not more than 3 to 4 times daily

• Children under 2 years of age: Consult a doctor

• When using for anal itching, cleanse the affected area with mild soap and warm water and rinse thoroughly, gently dry by patting or blotting with bathroom tissue or soft cloth befor applying

• Children under 12: Consult a doctor before using for anal itching

Other Information

• Store at room temperature 15º-30ºC (59º-86ºF)

• Avoid excessive heat

• Tamper Evident. Do not use if seal is damaged.

Inactive Ingredients

Cetostearyl Alcohol, Glyceryl Monostearate SE, Methylchloroisothiazolinone, Propylene Glycol, Purified Water, Stearic Acid, Trolamine, White Petrolatum

Questions?

1-888-DYNAREX Monday-Friday, 9AM-5PM EST

Label

Hydrocortisone Cream 1%